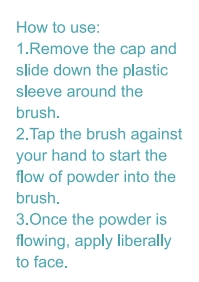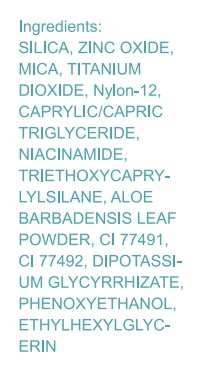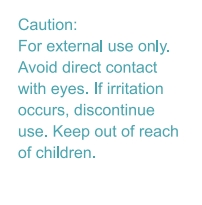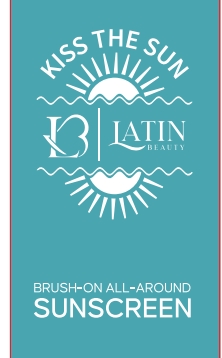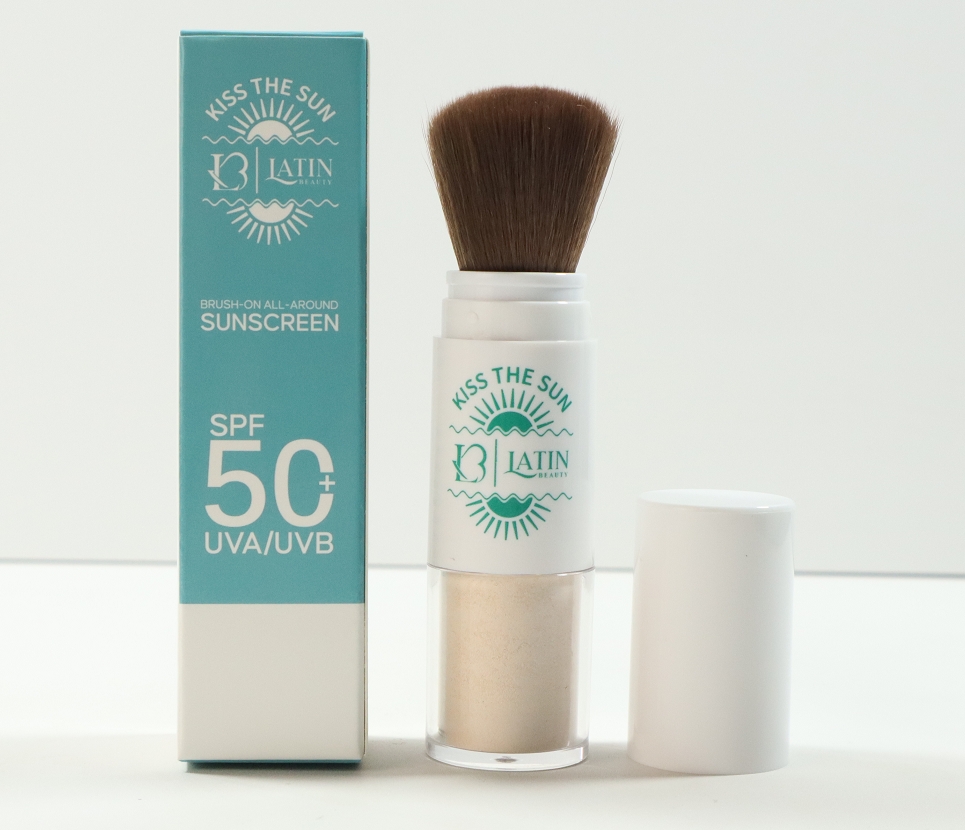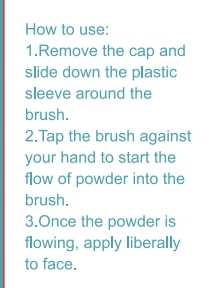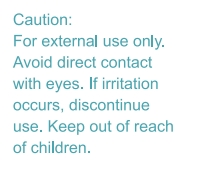 DRUG LABEL: Latin Beauty LLC. Powder Sunscreen SPF 50 Kiss the Sun
NDC: 85473-443 | Form: POWDER
Manufacturer: Guangzhou Yueyou Biological Technology Co., Ltd.
Category: otc | Type: HUMAN OTC DRUG LABEL
Date: 20250730

ACTIVE INGREDIENTS: TITANIUM DIOXIDE 0.9 g/6 g; ZINC OXIDE 1.32 g/6 g
INACTIVE INGREDIENTS: NYLON-12; CAPRYLIC/CAPRIC TRIGLYCERIDE; CI 77492; SILICA, TRIMETHYLSILYL CAPPED; CI 77491; MICA; NIACINAMIDE; ALOE BARBADENSIS LEAF POWDER; ETHYLHEXYLGLYCERIN; DIPOTASSIUM GLYCYRRHIZATE; PHENOXYETHANOL; TRIETHOXYCAPRYLYLSILANE

Latin Beauty LLC. Powder Sunscreen SPF 50 Kiss the Sun